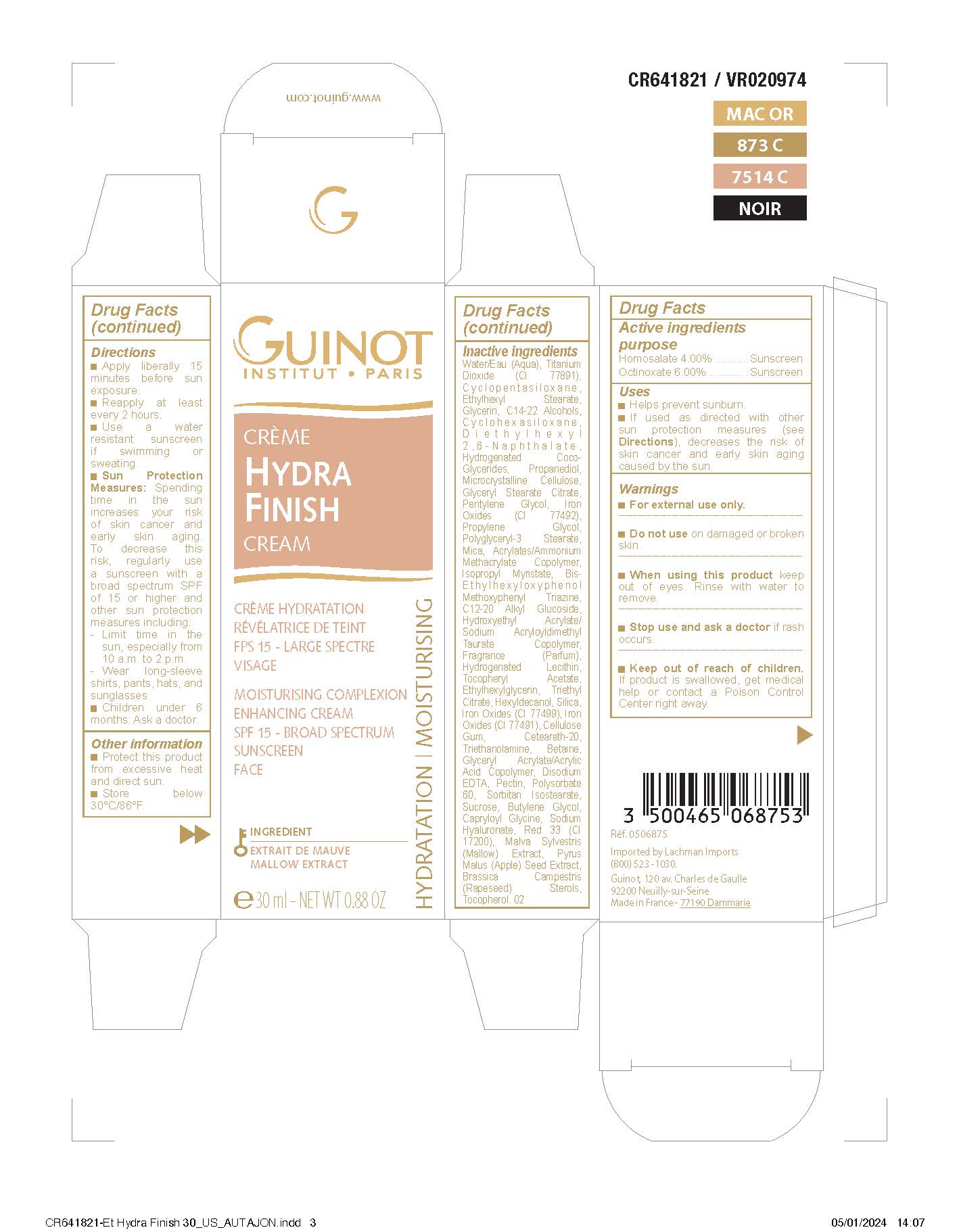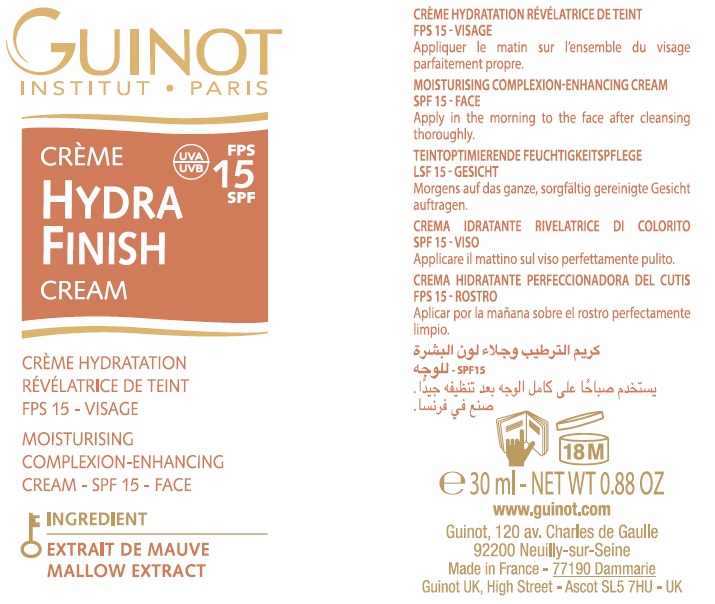 DRUG LABEL: Hydra Finish SPF 15
NDC: 54181-006 | Form: CREAM
Manufacturer: Guinot
Category: otc | Type: HUMAN OTC DRUG LABEL
Date: 20260129

ACTIVE INGREDIENTS: HOMOSALATE 40 mg/1 mL; OCTINOXATE 60 mg/1 mL
INACTIVE INGREDIENTS: WATER; TITANIUM DIOXIDE; CYCLOMETHICONE 5; ETHYLHEXYL STEARATE; GLYCERIN; C14-22 ALCOHOLS; CYCLOMETHICONE 6; DIETHYLHEXYL 2,6-NAPHTHALATE; HYDROGENATED COCO-GLYCERIDES; PROPANEDIOL; CELLULOSE, MICROCRYSTALLINE; GLYCERYL STEARATE CITRATE; PENTYLENE GLYCOL; FERRIC OXIDE YELLOW; PROPYLENE GLYCOL; MICA; ISOPROPYL MYRISTATE; BEMOTRIZINOL; C12-20 ALKYL GLUCOSIDE; HYDROXYETHYL ACRYLATE/SODIUM ACRYLOYLDIMETHYL TAURATE COPOLYMER (100000 MPA.S AT 1.5%); HYDROGENATED SOYBEAN LECITHIN; .ALPHA.-TOCOPHEROL ACETATE; ETHYLHEXYLGLYCERIN; TRIETHYL CITRATE; HEXYLDECANOL; SILICON DIOXIDE; FERROSOFERRIC OXIDE; FERRIC OXIDE RED; CARBOXYMETHYLCELLULOSE SODIUM, UNSPECIFIED FORM; POLYOXYL 20 CETOSTEARYL ETHER; TROLAMINE; BETAINE; PECTIN; POLYSORBATE 60; SORBITAN ISOSTEARATE; SUCROSE; BUTYLENE GLYCOL; CAPRYLOYL GLYCINE; HYALURONATE SODIUM; D&C RED NO. 33; MALVA SYLVESTRIS FLOWERING TOP; APPLE SEED; RAPESEED STEROL; TOCOPHEROL

Hydra Finish SPF 15

Active ingredients

Homosalate 4.0%

Octinoxate 6.0%

purpose

Sunscreen

Uses

- Helps prevent sunburn
- If used as directed with other sun protection measures (see Directions), decreases the risk of skin cancer and early skin aging caused by the sun

Warnings

- For external use only

Do not use

on damaged or broken skin

When using this product

keep out of eyes. Rinse with water to remove

Stop use and ask a doctor

if rash occurs

Keep out of reach of children.

If product is swallowed, get medical help or contact a Poison Control Center right away.

Directions

- Apply liberally 15 minutes before sun exposure
- Reapply at least every 2 hours
- Use a water resistant sunscreen if swimming or sweating
- Sun Protection Measures. Spending time in the sun increases your risk of skin cancer and early skin aging. To decrease this risk, regularly use a sunscreen with a broad spectrum SPF of 15 or higher and other sun protection measures including:
- Limit time in the sun, especially from 10 a.m. – 2 p.m.
- Wear long-sleeve shirts, pants, hats, and sunglasses
- Children under 6 months: Ask a doctor

Other information

- Protect this product from excessive heat and direct sun

Inactive ingredients

Water (Aqua), Titanium Dioxide (CI 77891), Cyclopentasiloxane, Ethylhexyl Stearate, Glycerin, C14- 22 Alcohols, Cyclohexasiloxane, Diethylhexyl 2,6-Naphthalate, Hydrogenated Coco-Glycerides, Propanediol, Microcrystalline Cellulose, Glyceryl Stearate Citrate, Pentylene Glycol, Iron Oxides (CI 77492), Propylene Glycol, Polyglyceryl-3 Stearate, Mica, Acrylates/Ammonium Methacrylate Copolymer, Isopropyl Myristate, Bis-Ethylhexyloxyphenol Methoxyphenyl Triazine, C12-20 Alkyl Glucoside, Hydroxyethyl Acrylate/Sodium Acryloyldimethyl Taurate Copolymer, Fragrance (Parfum), Hydrogenated Lecithin, Tocopheryl Acetate, Ethylhexylglycerin, Triethyl Citrate, Hexyldecanol, Silica, Iron Oxides (CI 77499), Iron Oxides (CI 77491), Cellulose Gum, Ceteareth-20, Triethanolamine, Betaine, Glyceryl Acrylate/Acrylic Acid Copolymer, Disodium EDTA, Pectin, Polysorbate 60, Sorbitan Isostearate, Sucrose, Butylene Glycol, Capryloyl Glycine, Sodium Hyaluronate, Red 33 (CI 17200), Malva Sylvestris (Mallow) Extract, Pyrus Malus (Apple) Seed Extract, Brassica Campestris (Rapeseed) Sterols, Tocopherol. 01